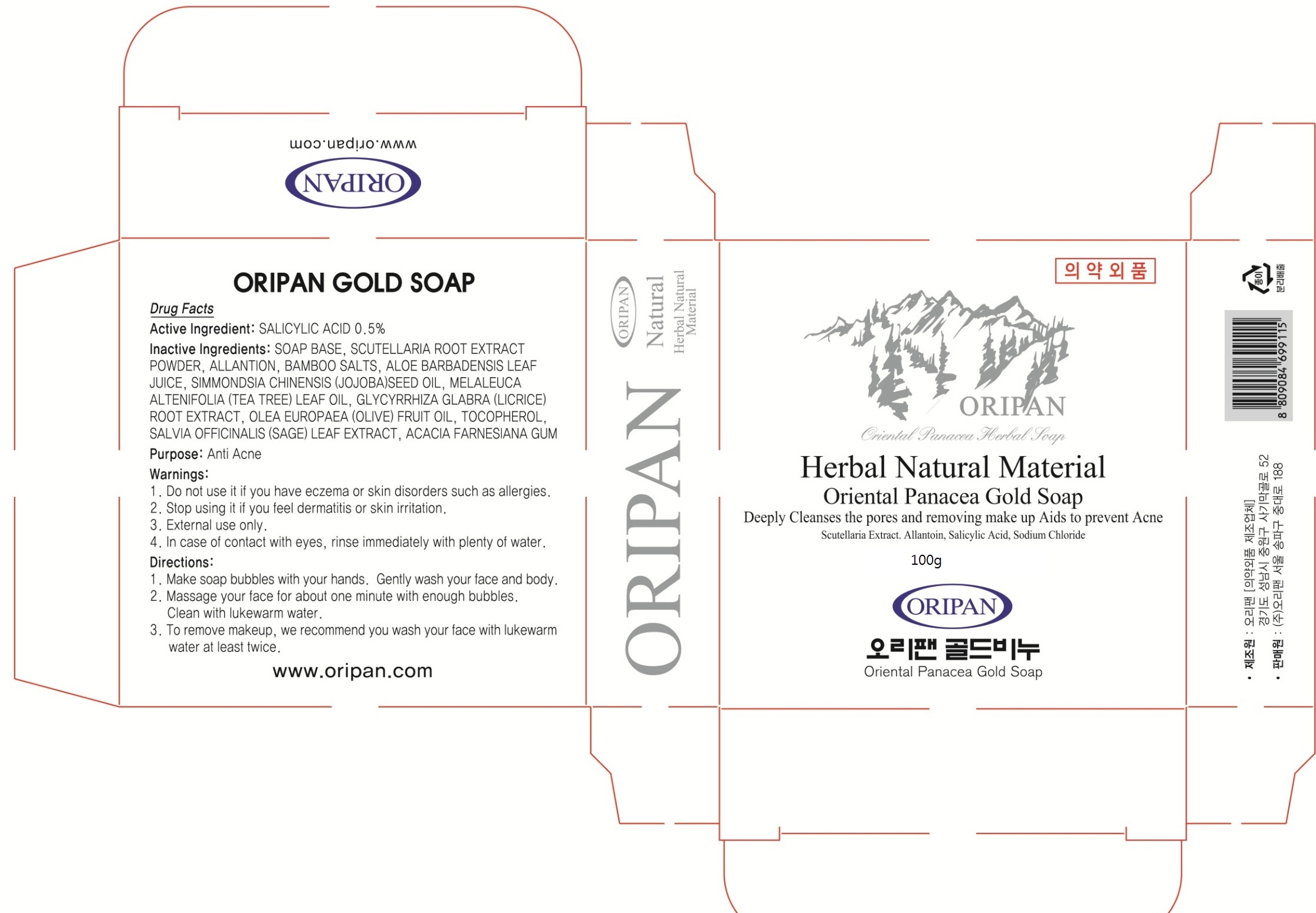 DRUG LABEL: ORIPAN GOLD 100g
NDC: 71109-030 | Form: SOAP
Manufacturer: ORIPAN CORPORATION. KOREA
Category: otc | Type: HUMAN OTC DRUG LABEL
Date: 20161215

ACTIVE INGREDIENTS: SALICYLIC ACID 0.50 g/100 g
INACTIVE INGREDIENTS: SCUTELLARIA BAICALENSIS ROOT; ALLANTOIN

ACTIVE INGREDIENT

Active Ingredient: SALICYLIC ACID 0.5%

INACTIVE INGREDIENT

Inactive Ingredients: SOAP BASE, SCUTELLARIA ROOT EXTRACT POWDER, ALLANTOIN, BAMBOO SALTS, ALOE BARBADENSIS LEAF JUICE, SIMMONDSIA CHINENSIS (JOJOBA)SEED OIL, MELALEUCA ALTENIFOLIA (TEA TREE) LEAF OIL, GLYCYRRHIZA GLABRA (LICRICE) ROOT EXTRACT, OLEA EUROPAEA (OLIVE) FRUIT OIL, TOCOPHEROL, SALVIA OFFICINALIS (SAGE) LEAF EXTRACT, ACACIA FARNESIANA GUM

PURPOSE

Purpose: Anti Acne

WARNINGS

Warnings: 1. Do not use it if you have eczema or skin disorders such as allergies.

2. Stop using it if you feel dermatitis or skin irritation.

3. External use only.

4. In case of contact with eyes, rinse immediately with plenty of water.

KEEP OUT OF REACH OF CHILDREN

Directions

Directions: 1. Make soap bubbles with your hands. Gently wash your face and body. 2. Massage your face for about one minute with enough bubbles. Clean with lukewarm water. 3. To remove makeup, we recommend you wash your face with lukewarm water at least twice.

Directions

Directions: 1. Make soap bubbles with your hands. Gently wash your face and body. 2. Massage your face for about one minute with enough bubbles. Clean with lukewarm water. 3. To remove makeup, we recommend you wash your face with lukewarm water at least twice.